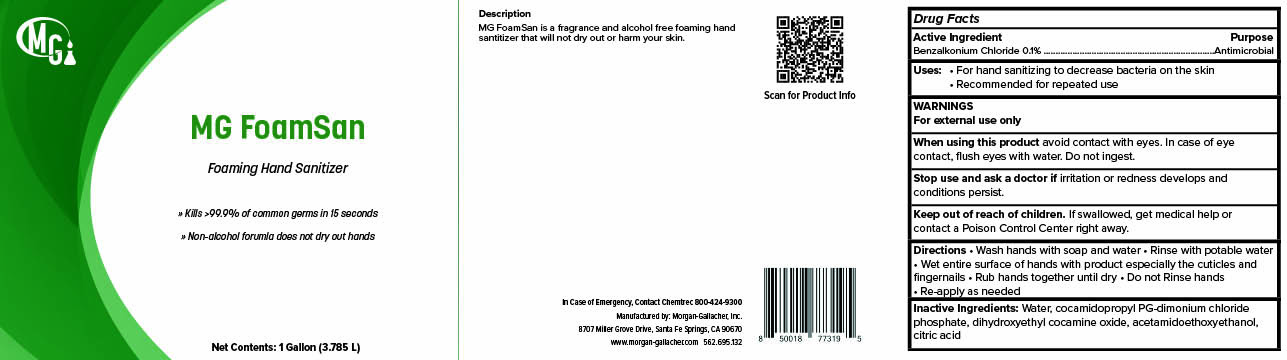 DRUG LABEL: MG FoamSan
NDC: 50241-522 | Form: LIQUID
Manufacturer: Morgan Gallacher Inc. DBA Custom Chemical Formulators Inc.
Category: otc | Type: HUMAN OTC DRUG LABEL
Date: 20251229

ACTIVE INGREDIENTS: BENZALKONIUM CHLORIDE 0.1 g/100 g
INACTIVE INGREDIENTS: WATER; COCAMIDOPROPYL PG-DIMONIUM CHLORIDE PHOSPHATE; DIHYDROXYETHYL COCAMINE OXIDE; ACETAMIDOETHOXYETHANOL; CITRIC ACID MONOHYDRATE

MG FoamSan

ACTIVE INGREDIENT

Benzalkonium Chloride ...........0.1%

Purpose

Antimicrobial

Uses

For hand sanitizing to decrease bacteria on the skin.

recommended for repeated use.

Warnings

For external use only.

When Using this Product

- Avoid contact with eyes.

- In case of eye contact, flush eyes with water.

Stop use and ask a doctor if

-Irritation or redness develops, if condition persists for more than 72 hours.

Keep out of reach of children. If swallowed, get medical help

or contact a Poison Control Center immediately.

Directions

-Pump a small amount of foam into palm of hand.

-Rub thoroughly over all surfaces of both hands.

-Rub hands together brisky until dry

Inactive Ingredients

Water, Cocamidopropyl PG-dimonium Chloride Phosphate, Dihydroxyethyl cocamine oxide, acetamidoethoxyethanol, citric acid.